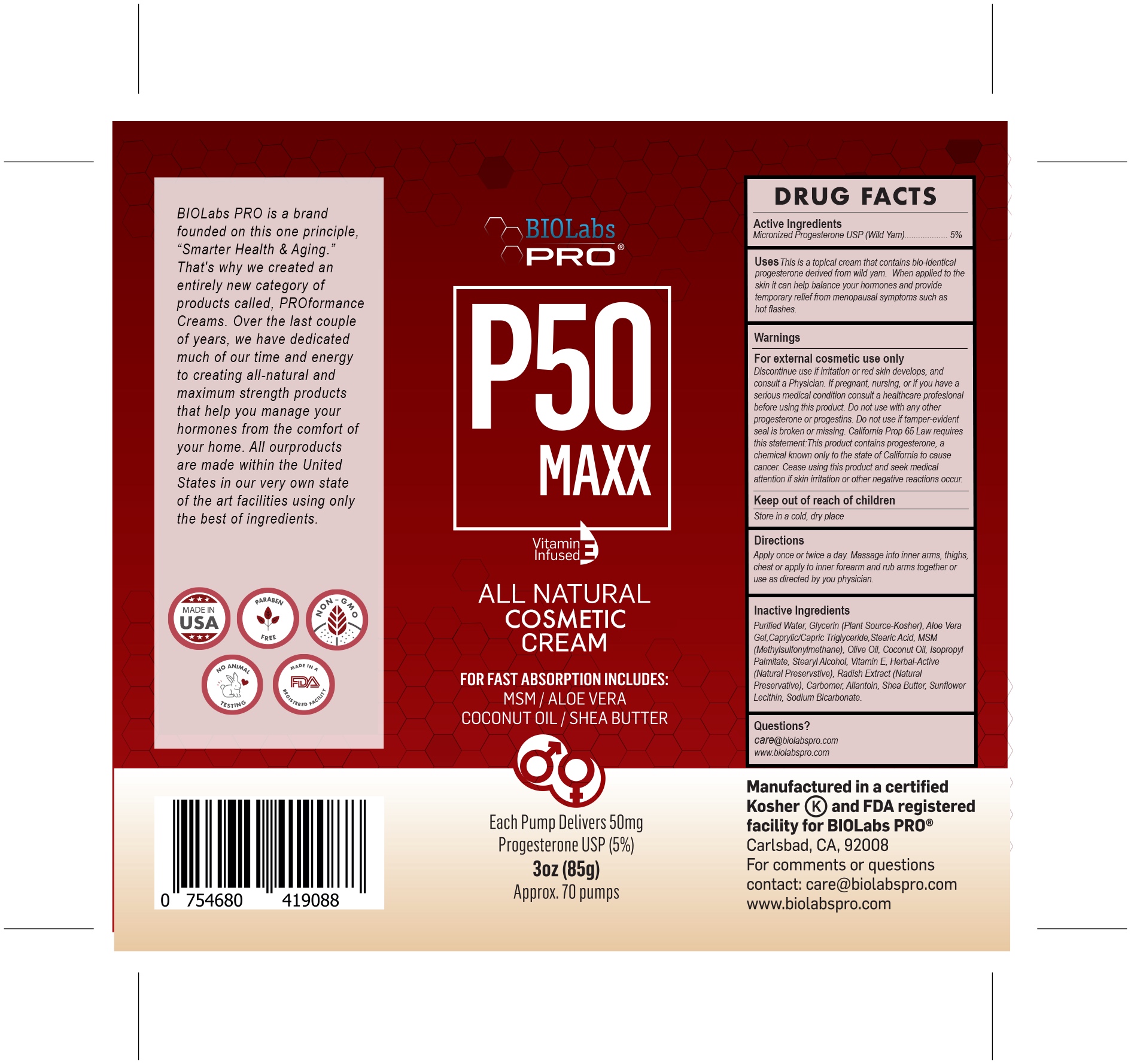 DRUG LABEL: P50 Progesterone Cream
NDC: 82018-0012 | Form: CREAM
Manufacturer: SHYNE BRANDS
Category: otc | Type: HUMAN OTC DRUG LABEL
Date: 20250601

ACTIVE INGREDIENTS: PROGESTERONE 1 mg/1 mg
INACTIVE INGREDIENTS: ALLANTOIN 1 mg/1 mg; GLYCERIN 1 mg/1 mg; ISOPROPYL PALMITATE 1 mg/1 mg; STEARIC ACID 1 mg/1 mg; LECITHIN, SUNFLOWER 1 mg/1 mg; SHEA BUTTER 1 mg/1 mg; ALOE VERA LEAF 1 mg/1 mg; OLIVE OIL 1 mg/1 mg; COCONUT OIL 1 mg/1 mg; SODIUM BICARBONATE 1 mg/1 mg

P50 Progesterone Cream

DRUG FACTS

Active Ingredients

Micronizrd Progesterone USP (Wild Yam) 5%

PURPOSE

This is a topical cream that contains bio-identical progesterone derived from wild yam. When applied to the skin it can help balance your hormones and provide temporary relief from menopausal symptoms such as hot flashes.

INDICATIONS AND USAGE

DIRECTIONS: Apply once or twice a day. Massage into inner arms, thighs, chest or apply to inner forearm and rub arms together or use as directed by your Physician.

THIS CONTAINER Yields approximately 70 full pumps or 50 mg of bio-identical Progesterone USP (5%) per pump. This is an All Natural product. Application is intended for external cosmetic use.

WARNINGS

WARNING: FOR EXTERNAL COSMETIC USE ONLY. Discontinue use if irritation or red skin develops, and consult a Physician. If pregnant, nursing, or if you have a serious medical condition consult a healthcare professional before using this product. Do not use with any other progesterone or progestins. Do not use if tamper-evident seal is broken or missing. California Prop 65 Law requires this statement: This product contains progesterone, a chemical known only to the State of California to cause cancer. Cease using this product and seek medical attention if skin irritation or other negative reactions occur. KEEP OUT OF REACH OF CHILDREN.

PREGNANCY OR BREAST FEEDING

If pregnant or nursing or if you have a serious medical condition consult a healthcare professional before using this product.

Keep Out of Reach of Children.

DOSAGE AND ADMINISTRATION

Apply once or twice a day. Massage into inner arms, thighs, chest or apply to inner forearm and rub arms together or use as directed by you physician.

INACTIVE INGREDIENT

Purified Water, Glycerin (Plant source - kosher) Aloe Vera Gel, Caprylic/Capric Triglyceride, Stearic Acid, MSM (Methylsulfonylmethane), Olive Oil, Coconut Oil, Isopropyl Palmitate, Stearyl Alcohol, Vitamin E, Blend of Essential oils and herbs (Natural Preservative), Radish Extract (Natural Preservative) Carbomer Allantoin Shea Butter Sunflower Lecithin Sodium Bicarbonate.

Questions?

care@biolabspro.com

www.biolabspro.com